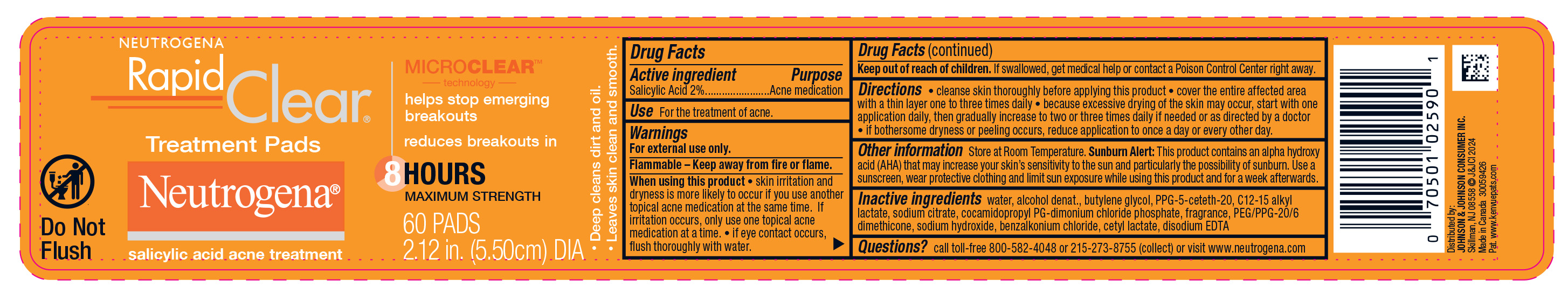 DRUG LABEL: Neutrogena Rapid Clear Treatment Pads
NDC: 69968-0719 | Form: CLOTH
Manufacturer: Kenvue Brands LLC
Category: otc | Type: HUMAN OTC DRUG LABEL
Date: 20250206

ACTIVE INGREDIENTS: SALICYLIC ACID 20 mg/1 1
INACTIVE INGREDIENTS: ALCOHOL; C12-15 ALKYL LACTATE; BENZALKONIUM CHLORIDE; BUTYLENE GLYCOL; PPG-5-CETETH-20; SODIUM CITRATE; COCAMIDOPROPYL PG-DIMONIUM CHLORIDE PHOSPHATE; PEG/PPG-20/6 DIMETHICONE; SODIUM HYDROXIDE; CETYL LACTATE; EDETATE DISODIUM ANHYDROUS; WATER

Neutrogena Rapid Clear Treatment Pads

Drug Facts

Active ingredient

Salicylic Acid 2%

Purpose

Acne medication

Use

For the treatment of acne.

Warnings

For external use only.

Flammable

Flammable – Keep away from fire or flame.

When using this product

• skin irritation and dryness is more likely to occur if you use another topical acne medication at the same time. If irritation occurs, only use one topical acne medication at a time. • if eye contact occurs, flush thoroughly with water.

Keep out of reach of children. If swallowed, get medical help or contact a Poison Control Center right away.

Directions

• cleanse skin thoroughly before applying this product • cover the entire affected area with a thin layer one to three times daily • because excessive drying of the skin may occur, start with one application daily, then gradually increase to two or three times daily if needed or as directed by a doctor • if bothersome dryness or peeling occurs, reduce application to once a day or every other day.

Other information

Store at Room Temperature. Sunburn Alert: This product contains an alpha hydroxy acid (AHA) that may increase your skin’s sensitivity to the sun and particularly the possibility of sunburn. Use a sunscreen, wear protective clothing and limit sun exposure while using this product and for a week afterwards.

Inactive ingredients

water, alcohol denat., butylene glycol, PPG-5-ceteth-20, C12-15 alkyl lactate, sodium citrate, cocamidopropyl PG-dimonium chloride phosphate, fragrance, PEG/PPG-20/6 dimethicone, sodium hydroxide, benzalkonium chloride, cetyl lactate, disodium EDTA

Questions?

call toll-free 800-582-4048 or 215-273-8755 (collect) or visit www.neutrogena.com

Distributed by:
JOHNSON & JOHNSON CONSUMER INC.
Skillman, NJ 08558

PRINCIPAL DISPLAY PANEL - 60 Count Jar Label

NEUTROGENA

Rapid

Clear®

Treatment Pads

Do Not

Flush

Neutrogena®

salicylic acid acne treatment

MICROCLEARTM

technology

helps stop emerging

breakouts

reduces breakouts in

8 HOURS

MAXIMUM STRENGTH

- Deep cleans dirt and oil.
- Leaves skin clean and smooth.

60 PADS

2.12 in. (5.50cm) DIA